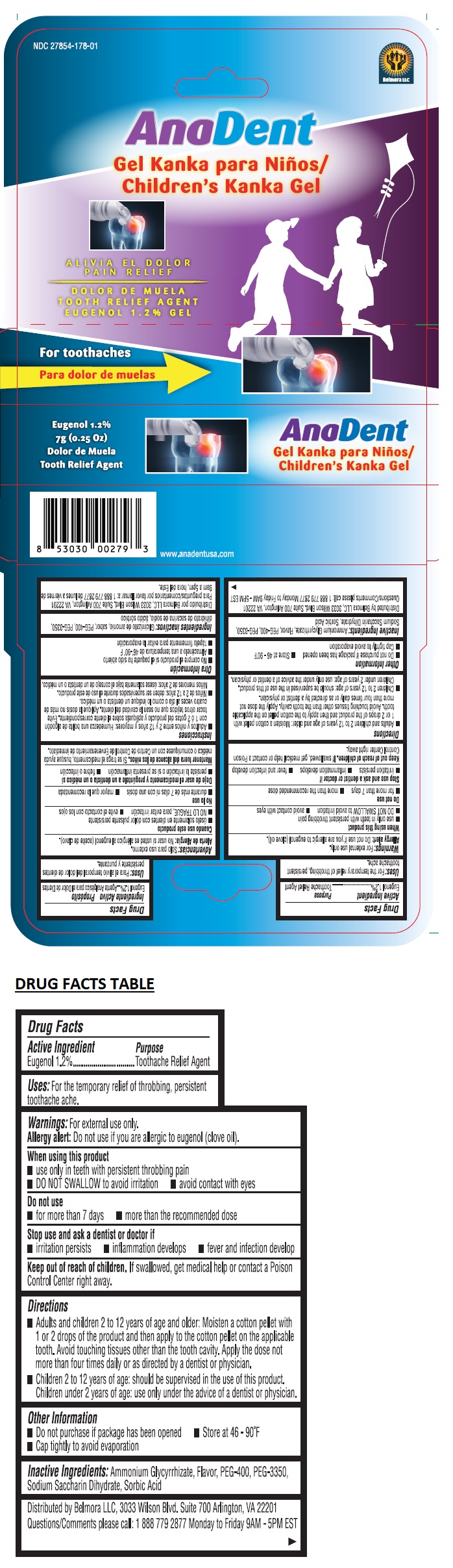 DRUG LABEL: AnaDent Childrens Kanka Gel
NDC: 27854-178 | Form: GEL
Manufacturer: Belmora LLC
Category: otc | Type: HUMAN OTC DRUG LABEL
Date: 20241004

ACTIVE INGREDIENTS: EUGENOL 12 mg/1 g
INACTIVE INGREDIENTS: AMMONIUM GLYCYRRHIZATE; POLYETHYLENE GLYCOL 400; POLYETHYLENE GLYCOL 3350; SACCHARIN SODIUM; SORBIC ACID

AnaDent Children's Kanka Gel

Active Ingredient

Eugenol 1.2%

Purpose

Toothache Relief Agent

Uses:

For the temporary relief of throbbing, persistent toothache.

Warnings:

For external use only.

Allergy alert: Do not use if you are allergic to eugenol (clove oil).

When using this product
• use only in teeth with persistent throbbing pain
• DO NOT SWALLOW to avoid irritation • avoid contact with eyes

Do not use
• for more than 7 days • more than the recommended dose

Stop use and ask a dentist or doctor if
• irritation persists • inflammation develops • fever and infection develop

Keep out of reach of children. If swallowed, get medical help or contact a Poison Control Center right away.

Directions

• Adults and children 2 to 12 years of age and older: Moisten a cotton pellet with 1 or 2 drops of the product and then apply to the cotton pellet on the applicable tooth. Avoid touching tissues other than the tooth cavity. Apply the dose not more than four times daily or as directed by a dentist or physician.
• Children 2 to 12 years of age: should be supervised in the use of this product. Children under 2 years of age: use only under the advice of a dentist or physician.

Other Information

• Do not purchase if package has been opened • Store at 46 - 90°F
• Cap tightly to avoid evaporation

Inactive Ingredients:

Ammonium Glycyrrhizate, Flavor, PEG-400, PEG-3350, Sodium Saccharin Dihydrate, Sorbic Acid

QUESTIONS

Questions/Comments please call: 1 888 779 2877 Monday to Friday 9AM - 5PM EST

PAIN RELIEF

For toothaches

Distributed by Belmora LLC, 3033 Wilson Blvd. Suite 700 Arlington, VA 22201

www.anadentusa.com